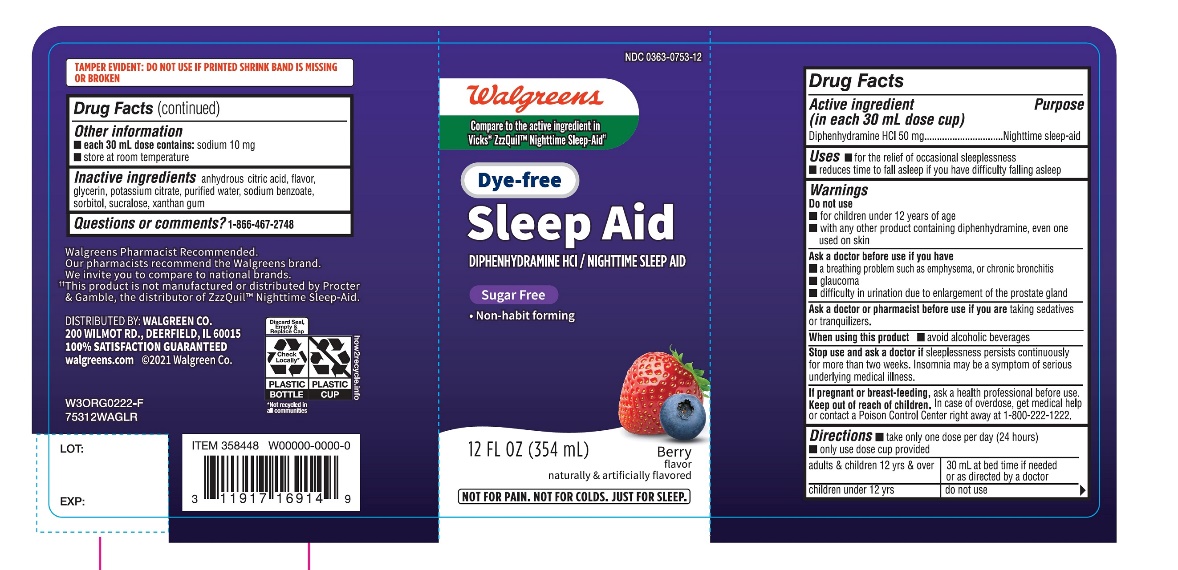 DRUG LABEL: Dye Free Wal Sleep Z
NDC: 0363-0753 | Form: LIQUID
Manufacturer: WALGREEN CO.
Category: otc | Type: HUMAN OTC DRUG LABEL
Date: 20251126

ACTIVE INGREDIENTS: DIPHENHYDRAMINE HYDROCHLORIDE 50 mg/30 mL
INACTIVE INGREDIENTS: ANHYDROUS CITRIC ACID; GLYCERIN; POTASSIUM CITRATE; WATER; SODIUM BENZOATE; SORBITOL; SUCRALOSE; XANTHAN GUM

Walgreens Dye-Free Wal -Sleep Z®Diphenhydramine HCl Nighttime Sleep Aid Berry Flavor 12 FL OZ (354 mL)

Drug Facts

Active ingredient (in each 30 mL)

Diphenhydramine HCl 50 mg

Purpose

Nighttime sleep-aid

Uses

- for the relief of occasional sleeplessness
- reduces time to fall asleep if you have difficulty falling asleep

Warnings

Do not use

- for children under 12 years of age
- with any other product containing diphenhydramine, even one used on skin

Ask a doctor before use if you have

- a breathing problem such as emphysema, or chronic bronchitis
- glaucoma
- difficulty in urination due to enlargement of the prostate gland

Ask a doctor or pharmacist before use if you aretaking sedatives or tranquilizers

When using this product

- avoid alcoholic beverages

Stop use and ask a doctor ifsleeplessness persists continuously for more than two weeks. Insomnia may be a symptom of serious underlying medical illness.

PREGNANCY OR BREAST FEEDING

If pregnant or breast-feeding, ask a health professional before use.

Keep out of reach of children.

In case of overdose, get medical help or contact a Poison Control Center right away at 1-800-222-1222.

Directions

- take only one dose per day (24 hours)
- measure with dosing cup provided

1. adults & children 12 yrs & over

1. One Dose = 30 mL at bed time if needed or as directed by a doctor

1. Children under 12 yrs

1. do not use

Other information

- each 30 mL dose contains: sodium 23 mg
- store at room temperature
- protect from light. Does not meet USP requirements for light-resistant packaging

Inactive ingredients

anhydrous citric acid, flavor, glycerin, potassium citrate, purified water, sodium benzoate, sorbitol, sucralose, xanthan gum.

Questions or comments?

1-866-467-2748

PRINCIPAL DISPLAY PANEL

Walgreens

Compare to Vicks®ZzzQuil®Nighttime Sleep-Aid active ingredient ††

NDC 0363-0753-12

Dye –Free

Wal-Sleep Z®

Diphenhydramine HCl / Nighttime Sleep Aid

DYE FREE

SUGAR FREE

- Non – habit forming

BERRY FLAVOR

12 FL OZ (354 mL)

NOT FOR TREATING COLD OR FLU,SEE WARNINGS.

FAILURE TO FOLLOW THESE WARNINGS COULD RESULT IN SERIOUS CONSEQUENCES.

TAMPER EVIDENT: DO NOT USE IF PRINTED SHRINK BAND IS MISSING OR BROKEN

Walgreens Pharmacist Recommended

Walgreens Pharmacist Survey

†† This product is not manufactured or distributed by Procter & Gamble, the distributor of ZzzQuil™ Nighttime Sleep-Aid.

DISTRIBUTED BY: WALGREEN CO.

200 WILMONT RD, DEERFIELD, IL 60015

100% SATISFACTION GUARANTEED

Walgreens.com ©2018 Walgreen Co.